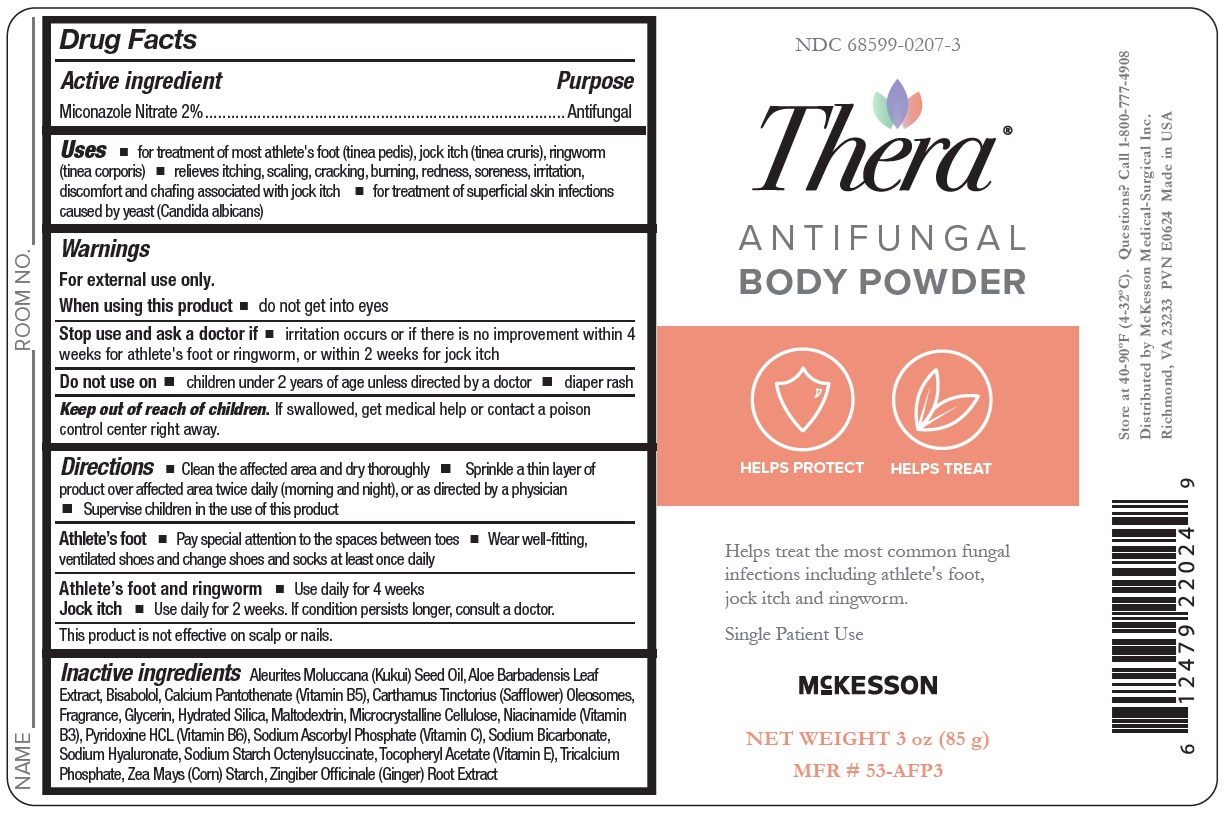 DRUG LABEL: THERA Antifungal Body
NDC: 68599-0207 | Form: POWDER
Manufacturer: McKesson Medical-Surgical Inc.
Category: otc | Type: HUMAN OTC DRUG LABEL
Date: 20240614

ACTIVE INGREDIENTS: MICONAZOLE NITRATE 20 mg/1 g
INACTIVE INGREDIENTS: TRICALCIUM PHOSPHATE; OCTENYLSUCCINIC ACID; CARTHAMUS TINCTORIUS SEED OLEOSOMES; CELLULOSE ACETATE; GLYCERIN; HYDRATED SILICA; SODIUM BICARBONATE; KUKUI NUT OIL; ALOE VERA LEAF; MALTODEXTRIN; NIACINAMIDE; PYRIDOXINE HYDROCHLORIDE; SODIUM ASCORBYL PHOSPHATE; .ALPHA.-TOCOPHEROL ACETATE, DL-; LEVOMENOL; HYALURONATE SODIUM; STARCH, CORN; GINGER OIL; CALCIUM PANTOTHENATE; MICROCRYSTALLINE CELLULOSE

Antifungal Body Powder

Active ingredient

Miconazole Nitrate 2.0%

Purpose

Antifungal

Keep out of reach of children.

If swallowed, get medical help or contact a Poison Control Center right away.

Uses

- for the treatment of athlete's foot (tinea pedis), jock itch (tinea cruris), ringworm (tinea corporis)
- relieves itching, scaling, cracking, burning, redness, soreness, irritation, discomfort and chafing associated with jock itch

Warnings

For external use only

Do not use on

- children under 2 years of age unless directed by a doctor

When using this product

- avoid contact with eyes

Stop use and ask a doctor if

- for athlete's foot and ringworm - irritation occurs or if there is no improvement within 4 weeks
- for jock itch - irritation occurs or if there is no improvement within 2 weeks.

Directions

- Clean the affected area and dry thoroughly
- Apply a thin layer of the product over affected area twice daily (morning and night) or as directed by a doctor
- Supervise children in the use of this product
- For athlete's foot: Pay special attention to spaces between the toes; wear well-fitting ventilated shoes, and change shoes and socks at least once daily
- For athlete's foot and ringworm, use daily for 4 weeks
- For jock itch, use daily for 2 weeks
- If condition persists longer, consult a doctor. This product is not effective on the scalp or nails

Other information

- Protect from freezing. Avoid excessive heat.

Inactive ingredients

Aleurites Moluccana (Kukui) Seed Oil, Aloe Barbadensis Leaf
Extract, Bisabolol, Calcium Pantothenate (Vitamin B5), Carthamus Tinctorius (Safflower) Oleosomes,
Fragrance, Glycerin, Hydrated Silica, Maltodextrin, Microcrystalline Cellulose, Niacinamide (Vitamin
B3), Pyridoxine HCL (Vitamin B6), Sodium Ascorbyl Phosphate (Vitamin C), Sodium Bicarbonate,
Sodium Hyaluronate, Sodium Starch Octenylsuccinate, Tocopheryl Acetate (Vitamin E), Tricalcium
Phosphate, Zea Mays (Corn) Starch, Zingiber Officinale (Ginger) Root Extract

Principal Display Panel

NDC 68599-0207-3

Thera

Antifungal Body Powder

Helps treat the most common fungal
infections including athlete's foot,
jock itch and ringworm.
Single Patient Use

Net Weight

3 oz (85 g)

MFR# 53-AFP3